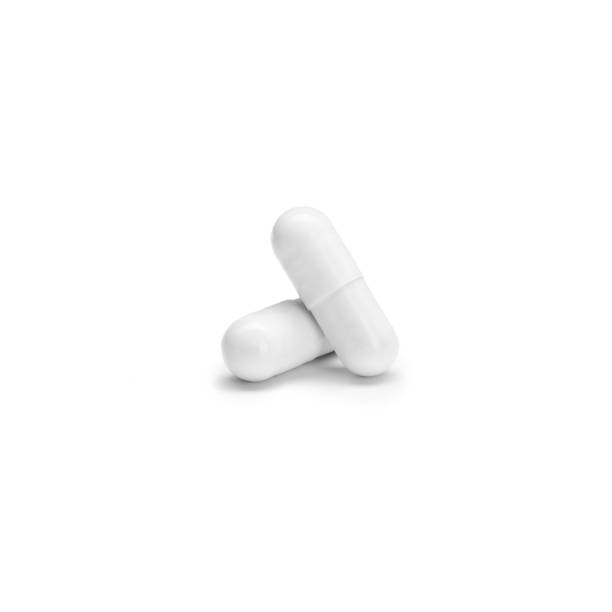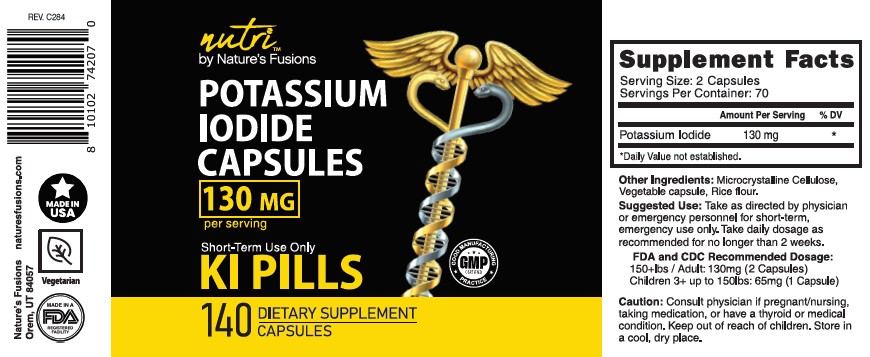 DRUG LABEL: Potassium Iodide
NDC: 73769-301 | Form: CAPSULE
Manufacturer: NATURE'S FUSIONS, LLC
Category: homeopathic | Type: HUMAN OTC DRUG LABEL
Date: 20231207

ACTIVE INGREDIENTS: POTASSIUM IODIDE 65 mg/1 1
INACTIVE INGREDIENTS: SILICON DIOXIDE; CELLULOSE, MICROCRYSTALLINE; MAGNESIUM STEARATE; CALCIUM PHOSPHATE, DIBASIC, DIHYDRATE; HYDROXYPROPYL CELLULOSE, UNSPECIFIED

Potassium Iodide

FDA and CDC Recommended Dosage

150+lbs / Adult: 130mg (2 Tablets)
Children 3+ up to 150lbs: 65mg (1 Tablet)

WARNINGS AND PRECAUTIONS

Consult physician if pregnant/nursing, taking medication, or have a thyroid or medical condition. Keep out of reach of children. Store in
a cool, dry place.

Caution:

Consult physician if pregnant/nursing, taking medication, or have a thyroid or medical condition. Keep out of reach of children. Store in
a cool, dry place.

Inactive Ingredients

Microcrystalline Cellulose, Magnesium Stearate, Silicon Dioxide

Suggested Use:

Take as directed by physician or emergency personnel for short-term, emergency use only. Take daily dosage as recommended for no longer than 2 weeks.

Caution:

Keep out of reach of children.

Suggested Use:

For short-term, emergency use only.

Active Ingredients

Potassium Iodide